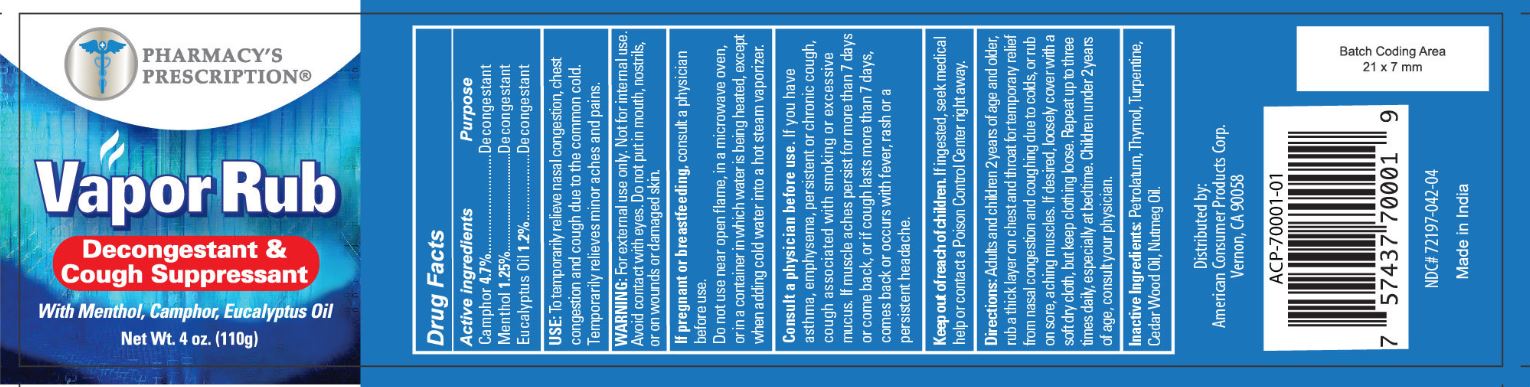 DRUG LABEL: Pharmacys Prescription Vapor Rub
NDC: 72197-046 | Form: GEL
Manufacturer: American Consumer Products Corp
Category: otc | Type: HUMAN OTC DRUG LABEL
Date: 20250331

ACTIVE INGREDIENTS: MENTHOL, UNSPECIFIED FORM 1.25 g/100 g; EUCALYPTUS OIL 1.2 g/100 g; CAMPHOR (SYNTHETIC) 4.7 g/100 g
INACTIVE INGREDIENTS: PETROLATUM; NUTMEG OIL; CEDAR LEAF OIL; TURPENTINE OIL; THYMOL

Pharmacy's Prescription 4 OZ Vapor Rub

Active Ingredient

Active Ingredients

Camphor 4.7%

Menthol 1.25%

Eucalyptus Oil 1.2%

Purpose

Decongestant

Decongestant

Decongestant

Indications & Usage

USE:

To temporarily relieve nasal congestion, chest congestion and cough due to the common cold. Temporarily relieves minor aches and pains.

Warning

Warning: For external use only. Not for internal use. Avoid contact with eyes. Do not put in mouth, nostrils, or on wounds or damaged skin.

If pregnant or breast feeding, consult a physician before use. Do not use near open flame, in a microwave oven or in a container in which water is being heated except when adding to cold water in a hot steam vaporizer.

Consult a physician before use. If you have asthma, emphysema, persistent or chronic cough associated with smoking or excessive mucus. If muscle aches persist for more than 7 days or comes back, or cough lasts more than 7 days, comes back or occurs with fever, rash or a persistent headache.

Keep out of reach of children. If ingested, get medical help or contact a Poison Control Center right away.

Dosage & Administration

Directions: Adults and children 2 years of age and older, rub a thick layer on chest and throat for temporary relief from nasal congestion and coughing due to colds, or rub on sore aching aching muscles. If desired, loosely cover with a soft dry cloth, but keep clothing loose. Repeat up to three times daily, especially at bedtime. Children under 2 years of age, consult your physician.

Inactive Ingredients

Inactive Ingredients: Petrolatum, Thymol, Turpentine, Cedar Wood Oil, Nutmeg Oil.